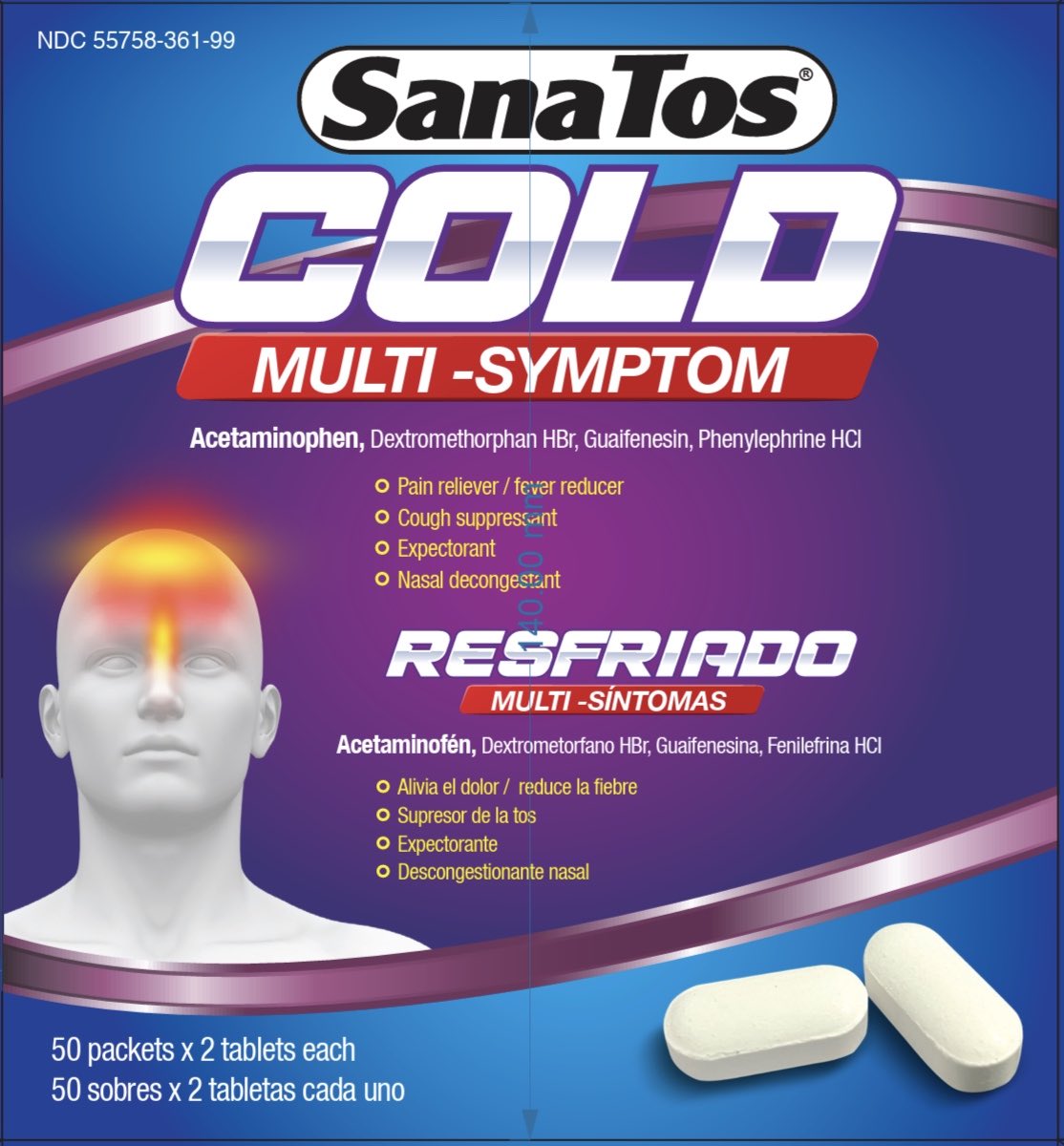 DRUG LABEL: SanaTos Multi Symptom
NDC: 55758-361 | Form: TABLET
Manufacturer: Pharmadel LLC
Category: otc | Type: HUMAN OTC DRUG LABEL
Date: 20250822

ACTIVE INGREDIENTS: ACETAMINOPHEN 325 mg/1 1; DEXTROMETHORPHAN HYDROBROMIDE 15 mg/1 1; GUAIFENESIN 200 mg/1 1; PHENYLEPHRINE HYDROCHLORIDE 5 mg/1 1
INACTIVE INGREDIENTS: WATER; SILICON DIOXIDE; STEARIC ACID; POVIDONE K30; TALC; STARCH, CORN; CELLULOSE, MICROCRYSTALLINE; CROSPOVIDONE

SanaTos MS Display 2x50 - Vovantis

Active Ingredient & Purposes

PURPOSE

Active ingredients (in each tablet) | Purposes
Acetaminophen 325 mg | Pain reliever/ fever reducer
Dextromethorphan HBr 15 mg | Cough suppressant
Guaifenesin 200 mg | Expectorant
Phenylephrine HCI 5 mg | Nasal decongestant

Uses

Temporarily relieves common cold/flu symptoms:

- cough due to minor throat and bronchial irritation
- minor aches and pain
- headache
- nasal congestion due to hay fever
- sore throat
- sinus congestion
- helps loosen phlegm (mucus) and thin bronchial secretions to make coughs more productive
- temporarily reduces fever

Warnings

Liver warning: This product contains acetaminophen. Severe liver damage may occur if you take

- more than 8 tablets in 24 hours, which is the maximum daily amount for this product
- with other drugs containing acetaminophen
- 3 or more alcoholic drinks every day while using this product

Allergy alert: Acetaminophen may cause severe skin reactions. Symptoms may include:

- skin reddening
- blisters
- rash If a skin reaction occurs, stop use and seek medical help right away.

Sore throat warning: If sore throat is severe, persists for more than 2 days, is accompanied or followed by fever, headache, rash, nausea, or vomiting, consult a doctor promptly.

Do not use

- with any other drug containing acetaminophen (prescription or nonprescription). If you are not sure whether a drug contains acetaminophen, ask a doctor or pharmacist.
- if you are now taking a prescription monoamine oxidase inhibitor (MAOI) (certain drugs for depression, psychiatric or emotional conditions, or Parkinson's disease), or for 2 weeks after stopping the MAOI drug. If you do not know if your prescription drug contains an MAOI, ask a doctor or pharmacist before taking this product.

Ask a doctor before use if you have

- liver disease
- heart disease
- high blood pressure
- thyroid disease
- diabetes
- trouble urinating due to enlarged prostate gland
- a cough that is accompanied by excessive phlegm (mucus)
- a persistent or chronic cough such as occurs with smoking, asthma, chronic bronchitis, or emphysema

Ask a doctor or pharmacist before use if you are

- taking the blood thinning drug warfarin

Stop use and ask a doctor if

- nervousness, dizziness, or sleeplessness occur
- redness or swelling is present
- pain gets worse or lasts more than 7 days
- fever gets worse or lasts more than 3 days
- new symptoms occur
- a persistent cough or symptoms do not improve within 7 days, tends to recur, or is accompanied by fever, rash, or persistent headache. These could be signs of a serious condition.

If pregnant or breast-feeding,

ask a health professional before use.

KEEP OUT OF REACH OF CHILDREN.

In case of overdose, get medical help or contact a Poison Control Center right away. Prompt medical attention is critical for adults as well as for children even if you do not notice any signs or symptoms.

Directions

- do not exceed recommended dosage
- adults and children 12 years of age and older:
- take 2 tablets every 6-8 hours; do not exceed 8 tablets in a 24-hour period
- children under 12 years of age: consult a doctor

Other information

- store at room temperature 59-86F (15-30C)
- avoid excessive heat and humidity
- Do not use if packet is open or torn.

Inactive ingredients

corn starch, microcrystalline cellulose, crospovidone, povidone k30, silicon dioxide, stearic acid, talc, water

Questions & comments?

+1-866-359-3478 (M-F) 9AM to 5 PM EST or www.pharmadel.com

Dist. by/ por:

PHARMADEL LLC

New Castle, DE 19720

Made in India/ Hecho en India